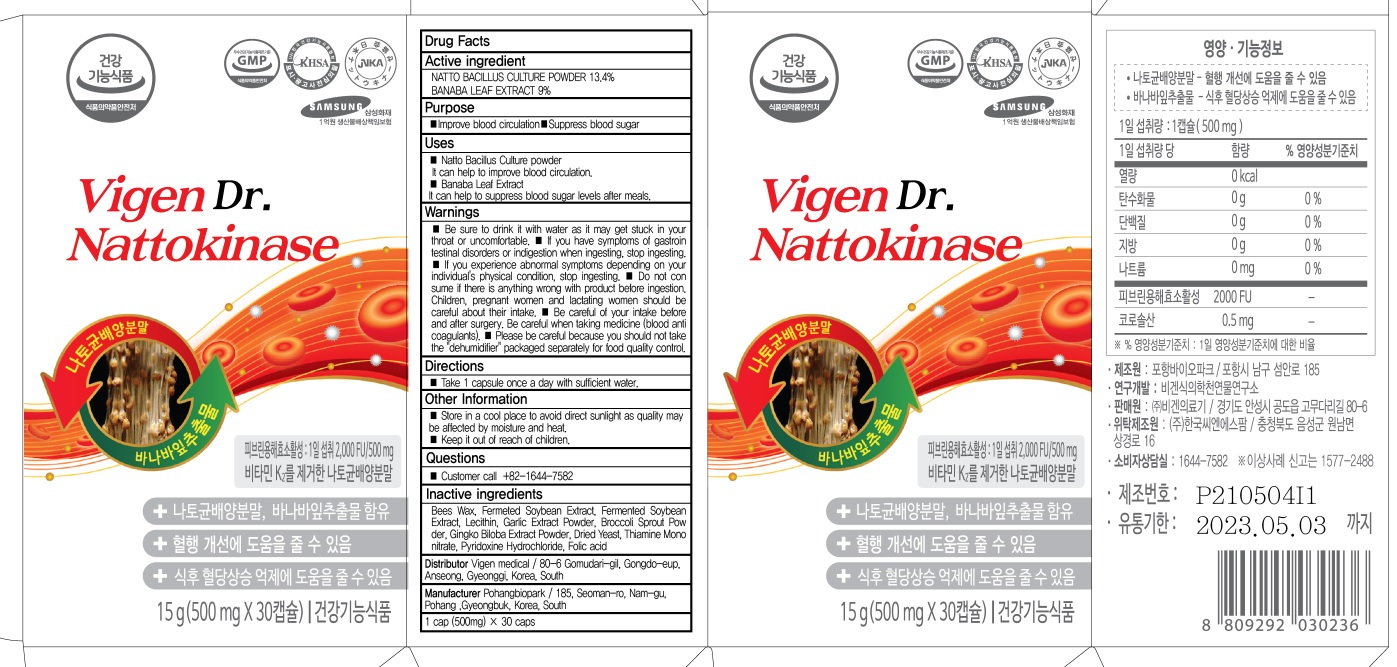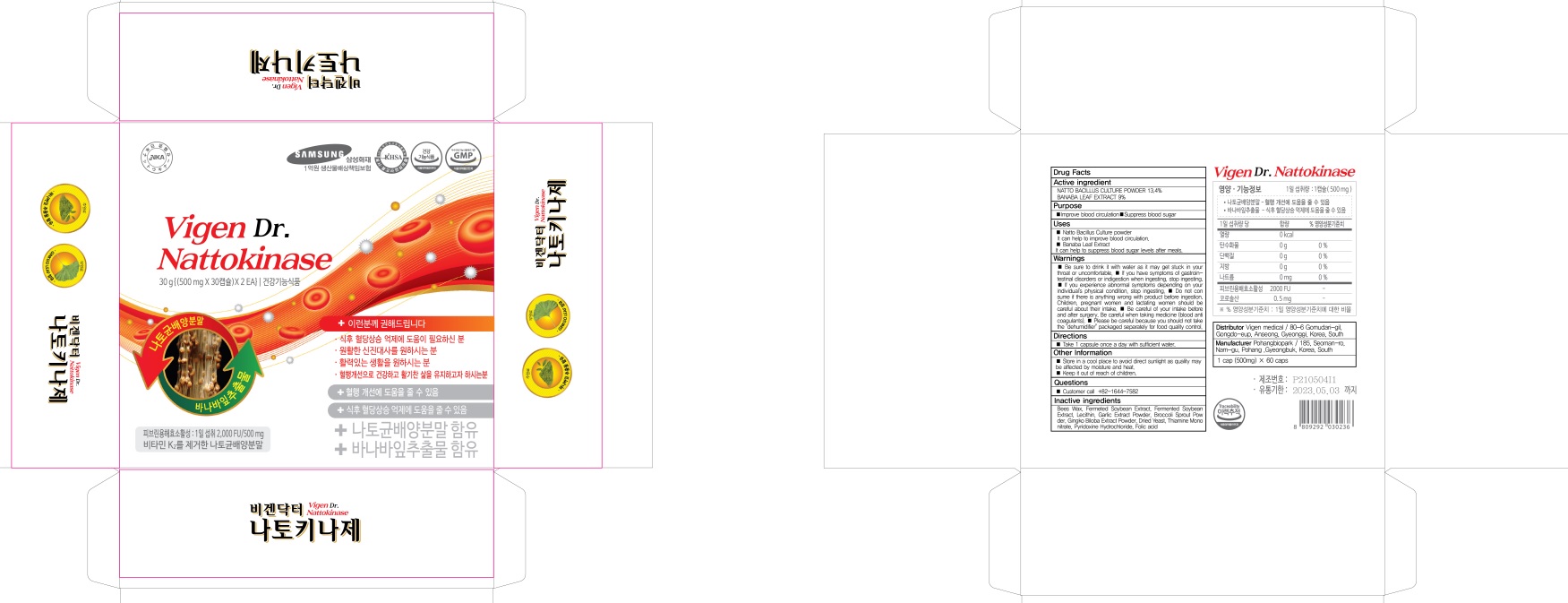 DRUG LABEL: Vigen Dr. Nattokinase
NDC: 82437-030 | Form: TABLET
Manufacturer: Vigen medical
Category: otc | Type: HUMAN OTC DRUG LABEL
Date: 20211215

ACTIVE INGREDIENTS: NATTOKINASE 67 mg/500 mg; LAGERSTROEMIA SPECIOSA LEAF 45 mg/500 mg
INACTIVE INGREDIENTS: YELLOW WAX; SOYBEAN OIL

ACTIVE INGREDIENT

NATTO BACILLUS CULTURE POWDER 13.4%
BANABA LEAF EXTRACT 9%

INACTIVE INGREDIENTS

Bees Wax, Fermeted Soybean Extract, Fermented Soybean Extract, Lecithin, Garlic Extract Powder, Broccoli Sprout Powder, Gingko Biloba Extract Powder, Dried Yeast, Thiamine Mononitrate, Pyridoxine Hydrochloride, Folic acid

PURPOSE

Improve blood circulation
Suppress blood sugar

WARNINGS

■ Be sure to drink it with water as it may get stuck in your throat or uncomfortable.
■ If you have symptoms of gastrointestinal disorders or indigestion when ingesting, stop ingesting.
■ If you experience abnormal symptoms depending on your individual's physical condition, stop ingesting.
■ Do not consume if there is anything wrong with product before ingestion. Children, pregnant women and lactating women should be careful about their intake.
■ Be careful of your intake before and after surgery. Be careful when taking medicine (blood anticoagulants).
■ Please be careful because you should not take the "dehumidifier" packaged separately for food quality control.

KEEP OUT OF REACH OF CHILDREN

Uses

■ Natto Bacillus Culture powder
It can help to improve blood circulation.
■ Banaba Leaf Extract
It can help to suppress blood sugar levels after meals.

Directions

■ Take 1 capsule once a day with sufficient water.

Other Information

■ Store in a cool place to avoid direct sunlight as quality may be affected by moisture and heat.
■ Keep it out of reach of children.

Questions

■ Customer call
+82-1644-7582